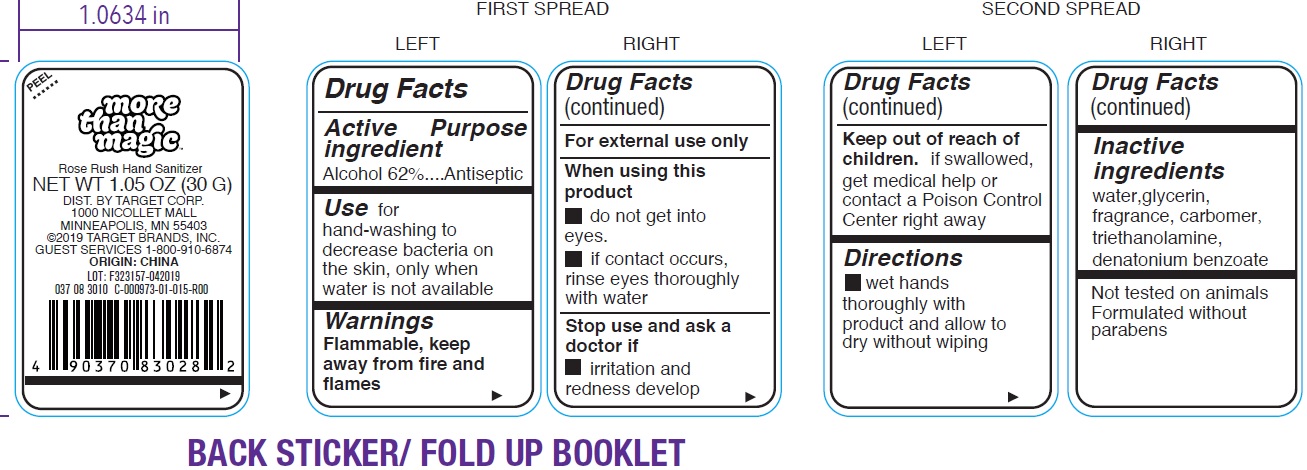 DRUG LABEL: rose rush hand sanitizer
NDC: 11673-865 | Form: GEL
Manufacturer: Target Corporation
Category: otc | Type: HUMAN OTC DRUG LABEL
Date: 20231026

ACTIVE INGREDIENTS: ALCOHOL 620 mg/1 g
INACTIVE INGREDIENTS: WATER; GLYCERIN; CARBOXYPOLYMETHYLENE; TROLAMINE; DENATONIUM BENZOATE

rose rush hand sanitizer

Active ingredient

Alcohol 62%

Purpose

Antiseptic

Use

for hand-washing to decrease bacteria on the skin, only when water is not available

Warnings

Flammable, keep away from fire or flame.

For external use only

When using this product

- do not get into eyes.
- if contact occurs, rinse eyes thoroughly with water

Stop use and ask a doctor if

irritation and redness develop

Keep out of reach of children.

if swallowed get medical help or contact a Poison Control Center right away.

Directions

- wet hands thoroughly with product and allow to dry without wiping

Inactive ingredients

water, glycerin, fragrance, carbomer, triethanolamine, denatonium benzoate.